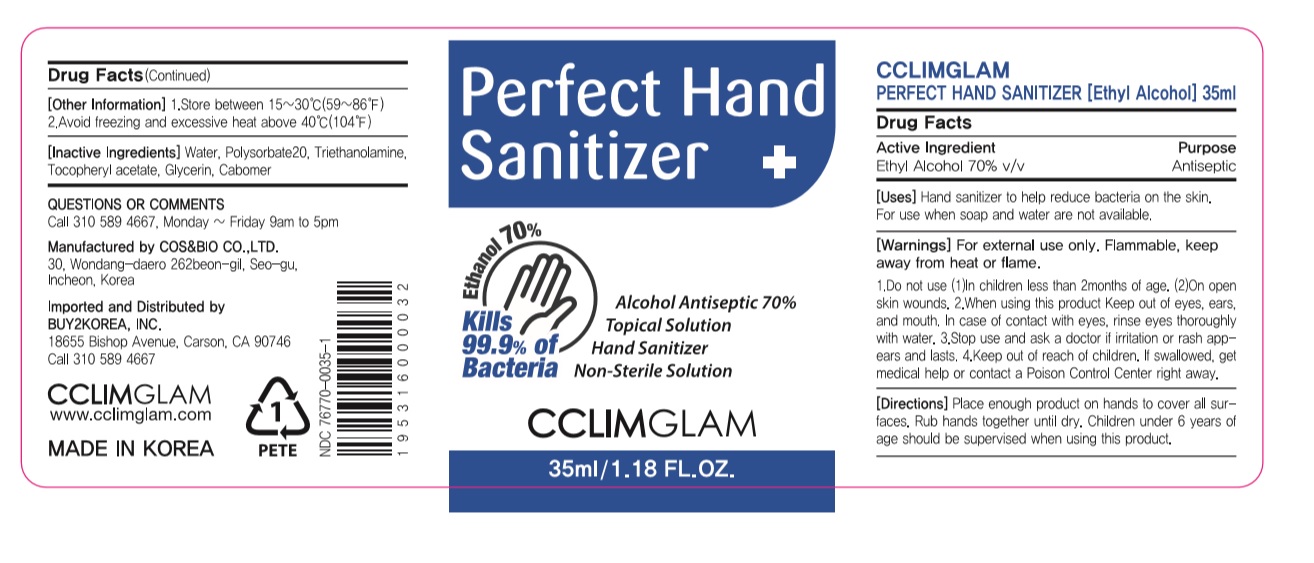 DRUG LABEL: CCLIMGLAM PERFECT HAND SANITIZER (Ethyl Alcohol)
NDC: 76770-0035 | Form: GEL
Manufacturer: COS&BIO Co Ltd
Category: otc | Type: HUMAN OTC DRUG LABEL
Date: 20200527

ACTIVE INGREDIENTS: ALCOHOL 24.5 mL/35 mL
INACTIVE INGREDIENTS: ALPHA-TOCOPHEROL ACETATE; GLYCERIN; CARBOMER HOMOPOLYMER, UNSPECIFIED TYPE; WATER; TROLAMINE; POLYSORBATE 20

[COS&BIO Co Ltd] CCLIMGLAM PERFECT HAND SANITIZER (Ethyl Alcohol)
76770-0035-1
35ml : Bottle+Cap